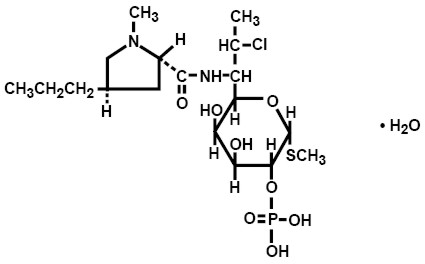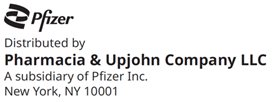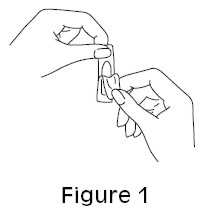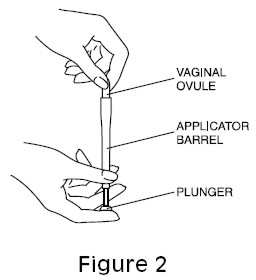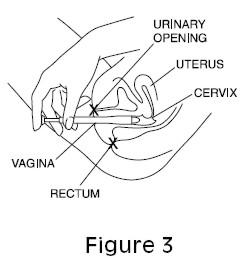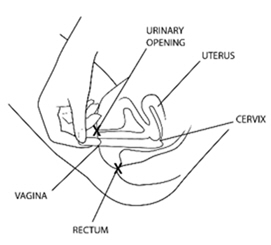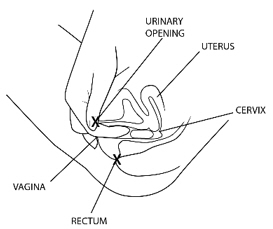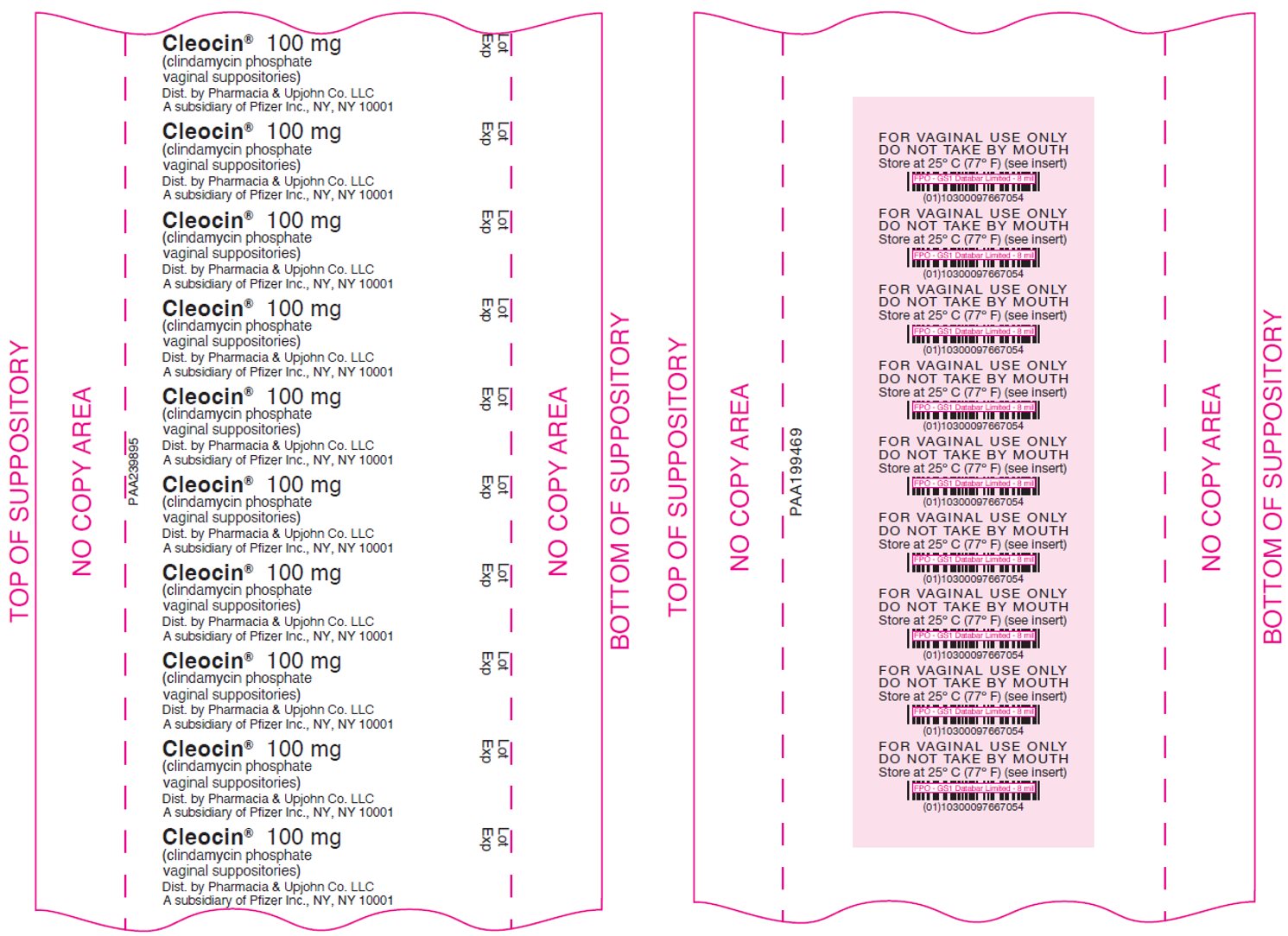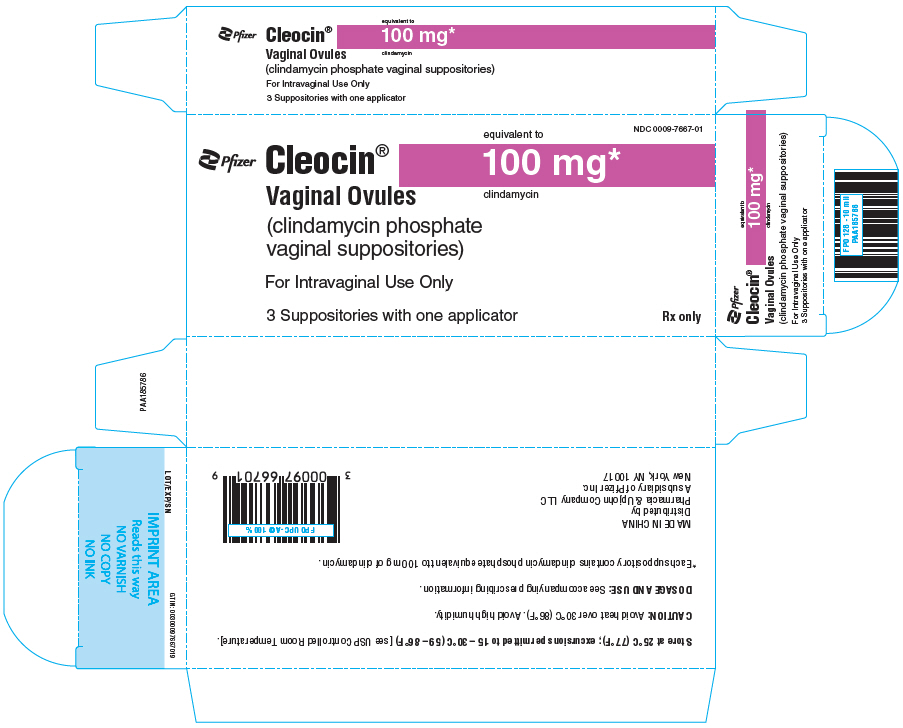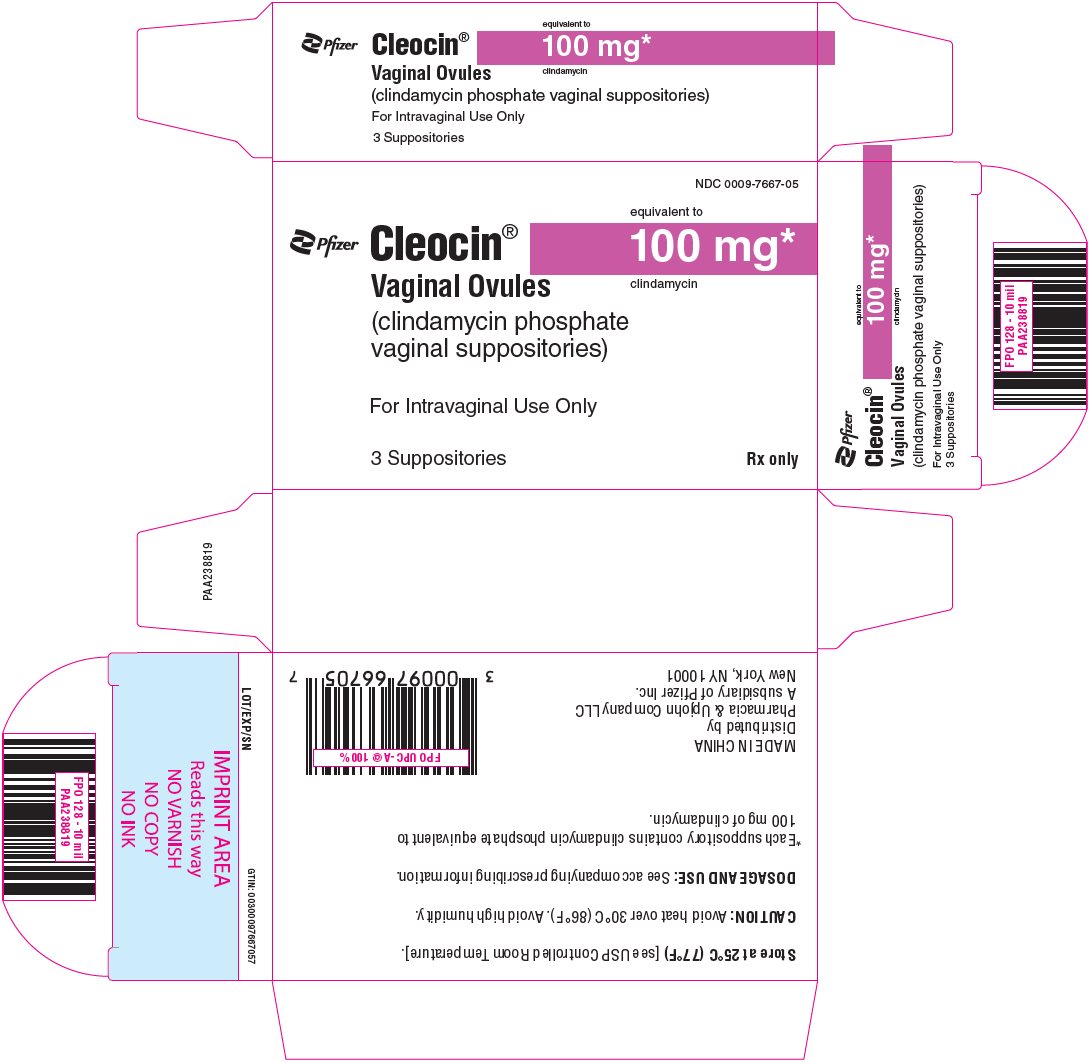 DRUG LABEL: Cleocin
NDC: 0009-7667 | Form: SUPPOSITORY
Manufacturer: Pharmacia & Upjohn Company LLC
Category: prescription | Type: HUMAN PRESCRIPTION DRUG LABEL
Date: 20251120

ACTIVE INGREDIENTS: CLINDAMYCIN PHOSPHATE 100 mg/1 1

Cleocin® Vaginal Ovules
(clindamycin phosphate vaginal suppositories)

FOR INTRAVAGINAL USE ONLY

DESCRIPTION

Clindamycin phosphate is a water-soluble ester of the semisynthetic antibiotic produced by a 7(S)-chloro-substitution of the 7(R)-hydroxyl group of the parent antibiotic lincomycin. The chemical name for clindamycin phosphate is methyl 7-chloro-6,7,8-trideoxy-6-(1-methyl-trans-4-propyl-L-2-pyrrolidinecarboxamido)-1-thio-L-threo-α-D-galacto-octopyranoside 2-(dihydrogen phosphate). The monohydrate form has a molecular weight of 522.98, and the molecular formula is C18H34ClN2O8PS•H2O. The structural formula is represented below:

CLEOCIN Vaginal Ovules are semisolid, white to off-white suppositories for intravaginal administration. Each 2.5 g suppository contains clindamycin phosphate equivalent to 100 mg clindamycin in a base consisting of a mixture of glycerides of saturated fatty acids.

CLINICAL PHARMACOLOGY

Mechanism of Action

Clindamycin is an antibacterial drug (See MICROBIOLOGY).

Pharmacokinetics

Systemic absorption of clindamycin was estimated following a once-a-day intravaginal dose of one clindamycin phosphate vaginal suppository (equivalent to 100 mg clindamycin) administered to 11 healthy female volunteers for 3 days. Approximately 30% (range 6% to 70%) of the administered dose was absorbed systemically on day 3 of dosing based on area under the concentration-time curve (AUC). Systemic absorption was estimated using a subtherapeutic 100 mg intravenous dose of clindamycin phosphate as a comparator in the same volunteers. The mean AUC following day 3 of dosing with the suppository was 3.2 µg hr/mL (range 0.42 to 11 µg hr/mL). The Cmax observed on day 3 of dosing with the suppository averaged 0.27 µg/mL (range 0.03 to 0.67 µg/mL) and was observed about 5 hours after dosing (range 1 to 10 hours). In contrast, the AUC and Cmax after the single intravenous dose averaged 11 µg hr/mL (range 5.1 to 26 µg hr/mL) and 3.7 µg/mL (range 2.4 to 5.0 µg/mL), respectively. The mean apparent elimination half-life after dosing with the suppository was 11 hours (range 4 to 35 hours) and is considered to be limited by the absorption rate.

The results from this study showed that systemic exposure to clindamycin (based on AUC) from the suppository was, on average, three-fold lower than that from a single subtherapeutic 100 mg intravenous dose of clindamycin. In addition, the recommended daily and total doses of intravaginal clindamycin suppository are far lower than those typically administered in oral or parenteral clindamycin therapy (100 mg of clindamycin per day for 3 days equivalent to about 30 mg absorbed per day from the ovule relative to 600 to 2700 mg/day for up to 10 days or more, orally or parenterally). The overall systemic exposure to clindamycin from Cleocin Vaginal Ovules is substantially lower than the systemic exposure from therapeutic doses of oral clindamycin hydrochloride (two-fold to 20-fold lower) or parenteral clindamycin phosphate (40-fold to 50-fold lower).

MICROBIOLOGY

Mechanism of Action

Clindamycin inhibits bacterial protein synthesis by binding to the 23S RNA of the 50S subunit of the ribosome. Clindamycin is predominantly bacteriostatic.

Although clindamycin phosphate is inactive in vitro, rapid in vivo hydrolysis converts it to active clindamycin.

Resistance

Resistance to clindamycin is most often caused by modification of the target site on the ribosome, usually by chemical modification of RNA bases or by point mutations in RNA or occasionally in proteins. Cross resistance has been demonstrated between lincosamides, macrolides and streptogramins B in some organisms. Cross resistance has been demonstrated between clindamycin and lincomycin.

Antibacterial Activity

Culture and sensitivity testing of bacteria are not routinely performed to establish the diagnosis of bacterial vaginosis (see INDICATIONS AND USAGE); standard methodology for the susceptibility testing of the potential bacterial pathogens, Gardnerella vaginalis, Mobiluncus spp., or Mycoplasma hominis, has not been defined.

The following in vitro data are available but their clinical significance is unknown. Clindamycin is active in vitro against most isolates of the following organisms reported to be associated with bacterial vaginosis:

- Bacteroides spp.
- Gardnerella vaginalis
- Mobiluncus spp.
- Mycoplasma hominis
- Peptostreptococcus spp.

INDICATIONS AND USAGE

CLEOCIN Vaginal Ovules are indicated for 3-day treatment of bacterial vaginosis in non-pregnant women. There are no adequate and well-controlled studies of CLEOCIN Vaginal Ovules in pregnant women.

NOTE: For purposes of this indication, a clinical diagnosis of bacterial vaginosis is usually defined by the presence of a homogeneous vaginal discharge that (a) has a pH of greater than 4.5, (b) emits a "fishy" amine odor when mixed with a 10% KOH solution, and (c) contains clue cells on microscopic examination. Gram's stain results consistent with a diagnosis of bacterial vaginosis include (a) markedly reduced or absent Lactobacillus morphology, (b) predominance of Gardnerella morphotype, and (c) absent or few white blood cells.

Other pathogens commonly associated with vulvovaginitis, e.g., Trichomonas vaginalis, Chlamydia trachomatis, Neisseria gonorrhoeae, Candida albicans, and herpes simplex virus, should be ruled out.

CONTRAINDICATIONS

CLEOCIN Vaginal Ovules are contraindicated in individuals with a history of hypersensitivity to clindamycin, lincomycin, or any of the components of this vaginal suppository. CLEOCIN Vaginal Ovules are also contraindicated in individuals with a history of regional enteritis, ulcerative colitis, or a history of "antibiotic-associated" colitis.

WARNINGS

Pseudomembranous colitis has been reported with nearly all antibacterial agents, including clindamycin, and may range in severity from mild to life-threatening. Orally and parenterally administered clindamycin has been associated with severe colitis, which may end fatally. Diarrhea, bloody diarrhea, and colitis (including pseudomembranous colitis) have been reported with the use of orally and parenterally administered clindamycin, as well as with topical (dermal and vaginal) formulations of clindamycin. Therefore, it is important to consider this diagnosis in patients who present with diarrhea subsequent to the administration of CLEOCIN Vaginal Ovules, because approximately 30% of the clindamycin dose is systemically absorbed from the vagina.

Treatment with antibacterial agents alters the normal flora of the colon and may permit overgrowth of clostridia. Studies indicate that a toxin produced by Clostridioides difficile is a primary cause of "antibiotic-associated" colitis.

After the diagnosis of pseudomembranous colitis has been established, therapeutic measures should be initiated. Mild cases of pseudomembranous colitis usually respond to discontinuation of the drug alone. In moderate to severe cases, consideration should be given to management with fluids and electrolytes, protein supplementation, and treatment with an antibacterial drug clinically effective against Clostridioides difficile colitis.

Onset of pseudomembranous colitis symptoms may occur during or after antimicrobial treatment.

PRECAUTIONS

General

The use of CLEOCIN Vaginal Ovules may result in the overgrowth of nonsusceptible organisms in the vagina. In clinical studies using CLEOCIN Vaginal Ovules, treatment-related moniliasis was reported in 2.7% and vaginitis in 3.6% of 589 nonpregnant women. Moniliasis, as reported here, includes the terms: vaginal or nonvaginal moniliasis and fungal infection. Vaginitis includes the terms: vulvovaginal disorder, vaginal discharge, and vaginitis/vaginal infection.

Information for the Patient

The patient should be instructed not to engage in vaginal intercourse or use other vaginal products (such as tampons or douches) during treatment with this product.

The patient should also be advised that these suppositories use an oleaginous base that may weaken latex or rubber products such as condoms or vaginal contraceptive diaphragms. Therefore, the use of such products within 72 hours following treatment with CLEOCIN Vaginal Ovules is not recommended.

Drug Interactions

Systemic clindamycin has been shown to have neuromuscular blocking properties that may enhance the action of other neuromuscular blocking agents. Therefore, it should be used with caution in patients receiving such agents.

Carcinogenesis, Mutagenesis, Impairment of Fertility

Long-term studies in animals have not been performed with clindamycin to evaluate carcinogenic potential. Genotoxicity tests performed included a rat micronucleus test and an Ames test. Both tests were negative. Fertility studies in rats treated orally with up to 300 mg/kg/day (31 times the human exposure based on mg/m^2) revealed no effects on fertility or mating ability.

Pregnancy

Teratogenic effects

In clinical trials with pregnant women, the systemic administration of clindamycin during the second and third trimesters, has not been associated with an increased frequency of congenital abnormalities.

Clindamycin vaginal ovules should be used during the first trimester of pregnancy only if clearly needed and the benefits outweigh the risks. There are no adequate and well-controlled studies of CLEOCIN Vaginal Ovules in pregnant women during the first trimester of pregnancy.

CLEOCIN Vaginal Cream, 2%, has been studied in pregnant women during the second trimester. In women treated for 7 days, abnormal labor was reported more frequently in patients who received CLEOCIN Vaginal Cream compared to those receiving placebo (1.1% vs. 0.5% of patients, respectively).

Reproduction studies have been performed in rats and mice using oral and parenteral doses of clindamycin up to 600 mg/kg/day (62 and 25 times, respectively, the maximum human dose based on body surface area) and have revealed no evidence of harm to the fetus due to clindamycin. Cleft palates were observed in fetuses from one mouse strain treated intraperitoneally with clindamycin at 200 mg/kg/day (about 10 times the recommended dose based on body surface area conversions). Since this effect was not observed in other mouse strains or in other species, the effect may be strain specific.

Nursing Mothers

Limited published data based on breast milk sampling reports that clindamycin appears in human breast milk in the range of less than 0.5 to 3.8 mcg/mL at dosages of 150 mg orally to 600 mg intravenously. It is not known if clindamycin is excreted in human breast milk following the use of vaginally administered clindamycin phosphate.

Clindamycin has the potential to cause adverse effects on the breast-fed infant's gastrointestinal flora. If clindamycin is required by a nursing mother, it is not a reason to discontinue breastfeeding, but an alternate drug may be preferred. Monitor the breast-fed infant for possible adverse effects on the gastrointestinal flora, such as diarrhea, candidiasis (thrush, diaper rash) or rarely, blood in the stool indicating possible antibiotic-associated colitis.

The developmental and health benefits of breastfeeding should be considered along with the mother's clinical need for clindamycin and any potential adverse effects on the breast-fed child from clindamycin or from the underlying maternal condition.

Pediatric Use

The safety and efficacy of CLEOCIN Vaginal Ovules in the treatment of bacterial vaginosis in post-menarchal females have been established on the extrapolation of clinical trial data from adult women. When a post-menarchal adolescent presents to a health professional with bacterial vaginosis symptoms, a careful evaluation for sexually transmitted diseases and other risk factors for bacterial vaginosis should be considered. The safety and efficacy of CLEOCIN Vaginal Ovules in pre-menarchal females have not been established.

Geriatric Use

Clinical studies of CLEOCIN Vaginal Ovules did not include sufficient numbers of subjects aged 65 and over to determine whether they respond differently from younger subjects.

ADVERSE REACTIONS

Clinical Trials

In clinical trials, 3 (0.5%) of 589 nonpregnant women who received treatment with CLEOCIN Vaginal Ovules discontinued therapy due to drug-related adverse events. Adverse events judged to have a reasonable possibility of having been caused by clindamycin phosphate vaginal suppositories were reported for 10.5% of patients. Events reported by 1% or more of patients receiving CLEOCIN Vaginal Ovules were as follows:

Urogenital system: Vulvovaginal disorder (3.4%), vaginal pain (1.9%), and vaginal moniliasis (1.5%).

Body as a whole: Fungal infection (1.0%).

Other events reported by <1% of patients included:

Urogenital system: Menstrual disorder, dysuria, pyelonephritis, vaginal discharge, and vaginitis/vaginal infection.

Body as a whole: Abdominal cramps, localized abdominal pain, fever, flank pain, generalized pain, headache, localized edema, and moniliasis.

Digestive system: Diarrhea, nausea, and vomiting.

Skin: Nonapplication-site pruritis, rash, application-site pain, and application-site pruritis.

Other clindamycin formulations

The overall systemic exposure to clindamycin from CLEOCIN Vaginal Ovules is substantially lower than the systemic exposure from therapeutic doses of oral clindamycin hydrochloride (two-fold to 20-fold lower) or parenteral clindamycin phosphate (40-fold to 50-fold lower). (See CLINICAL PHARMACOLOGY.) Although these lower levels of exposure are less likely to produce the common reactions seen with oral or parenteral clindamycin, the possibility of these and other reactions cannot be excluded.

The following adverse reactions and altered laboratory tests have been reported with the oral or parenteral use of clindamycin and may also occur following administration of CLEOCIN Vaginal Ovules:

Infections and Infestations: Clostridioides difficile colitis

Gastrointestinal: Abdominal pain, esophagitis, nausea, vomiting, diarrhea, and pseudomembranous colitis. (See WARNINGS.)

Hematopoietic: Transient neutropenia (leukopenia), eosinophilia, agranulocytosis, and thrombocytopenia have been reported. No direct etiologic relationship to concurrent clindamycin therapy could be made in any of these reports.

Hypersensitivity Reactions: Maculopapular rash and urticaria have been observed during drug therapy. Generalized mild to moderate morbilliform-like skin rashes are the most frequently reported of all adverse reactions. Cases of Acute Generalized Exanthematous Pustulosis (AGEP), erythema multiforme, some resembling Stevens-Johnson syndrome, have been associated with clindamycin. A few cases of anaphylactoid reactions have been reported. If a hypersensitivity reaction occurs, the drug should be discontinued.

Liver: Jaundice and abnormalities in liver function tests have been observed during clindamycin therapy.

Musculoskeletal: Cases of polyarthritis have been reported.

Renal: Acute kidney injury

Immune System: Drug reaction with eosinophilia and systemic symptoms (DRESS) cases have been reported.

There have been reports of pseudomembranous colitis following the administration of clindamycin vaginal cream.

OVERDOSAGE

Vaginally applied clindamycin phosphate contained in CLEOCIN Vaginal Ovules could be absorbed in sufficient amounts to produce systemic effects. (See WARNINGS and ADVERSE REACTIONS.)

DOSAGE AND ADMINISTRATION

The recommended dose is one CLEOCIN Vaginal Ovule (containing clindamycin phosphate equivalent to 100 mg clindamycin per 2.5 g suppository) intravaginally per day, preferably at bedtime, for 3 consecutive days.

HOW SUPPLIED

CLEOCIN Vaginal Ovules are supplied as follows:

Carton of three suppositories with one applicator | NDC 0009-7667-01
Carton of three suppositories without the applicator | NDC 0009-7667-05

STORAGE AND HANDLING

Important Information: Store at 25°C (77°F); excursions permitted to 15 – 30°C (59 – 86°F) [see USP Controlled Room Temperature].

Caution: Avoid heat over 30°C (86°F). Avoid high humidity. See end of carton for the lot number and expiration date.

Rx only

This product's labeling may have been updated. For the most recent prescribing information, please visit www.pfizer.com.

LAB-0047-16.0
Revised 03/2025

Cleocin® Vaginal Ovules (clindamycin phosphate vaginal suppositories)

DIRECTIONS FOR USE

How do I use CLEOCIN Vaginal Ovules?

For vaginal use only. Do not take by mouth.

Use one CLEOCIN Vaginal Ovule daily, preferably at bedtime, for 3 days in a row.

Do not use this product if the foiled pouches containing vaginal ovules are torn, opened, or incompletely sealed.

Read the full directions below before using.

Insertion with the applicator:

1. Remove the vaginal ovule from its packaging (See Figure 1).

2. Pull back the plunger about an inch and place the vaginal ovule in the wider end of the applicator barrel (See Figure 2).

3. Hold the applicator as shown and gently insert the end of the applicator into the vagina as far as it will go comfortably. This can be done while lying on your back with your knees bent (as shown in Figure 3), or while standing with your feet apart and your knees bent.

4. While holding the barrel of the applicator in place, push the plunger in until it stops to release the vaginal ovule. Remove the applicator from the vagina.
5. Clean the applicator after each use. Pull the two pieces apart and wash them with soap and warm water. Rinse well and dry. Put the two pieces back together and store in a clean, dry place.
6. Once inside the vagina, the ovule melts. Lie down as soon as possible. This will keep leakage to a minimum.
7. Repeat steps 1 through 6, before bedtime, for the next 2 days.

Insertion without the applicator:

1. Remove the vaginal ovule from its packaging (See Figure 1 above).
2. Holding the ovule with your thumb and a finger, insert it into the vagina (See Figure 4).
Figure 4
3. Using your finger, gently push the ovule into the vagina as far as it will comfortably go (See Figure 5).
Figure 5
4. Once inside the vagina, the ovule melts. Lie down as soon as possible. This will keep leakage to a minimum.
5. Repeat steps 1 through 4, before bedtime, for the next 2 days.

STORAGE CONDITIONS:

Store at 25°C (77°F); excursions permitted to 15 – 30°C (59 – 86°F) [see USP Controlled Room Temperature].

Caution: Avoid heat over 30°C (86°F). Avoid high humidity. See end of carton for the lot number and expiration date.

LAB-0649-3.0
Revised March 2025

PRINCIPAL DISPLAY PANEL - 100 mg Suppository Blister Pack

Cleocin®
100 mg
(clindamycin phosphate
vaginal suppositories)
Dist. by Pharmacia & Upjohn Co. LLC
A subsidiary of Pfizer Inc., NY, NY 10001

Lot
Exp

PRINCIPAL DISPLAY PANEL - 100 mg Suppository Blister Pack Carton

NDC 0009-7667-01

Pfizer

Cleocin®
Vaginal Ovules
(clindamycin phosphate
vaginal suppositories)

equivalent to
100 mg*
clindamycin

For Intravaginal Use Only

3 Suppositories with one applicator

Rx only

PRINCIPAL DISPLAY PANEL - 100 mg Suppository Blister Pack Carton - NDC 0009-7667-05

NDC 0009-7667-05

Pfizer

Cleocin®
Vaginal Ovules
(clindamycin phosphate
vaginal suppositories)

equivalent to
100 mg*
clindamycin

For Intravaginal Use Only

3 Suppositories

Rx only